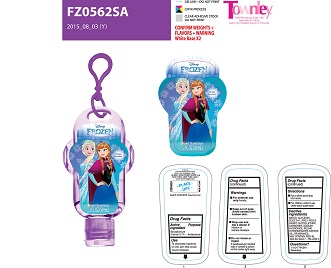 DRUG LABEL: Frozen Grape Hand Sanitizer
NDC: 54860-034 | Form: GEL
Manufacturer: shenzhen Lantern Science Co. Ltd.
Category: otc | Type: HUMAN OTC DRUG LABEL
Date: 20160613

ACTIVE INGREDIENTS: BENZALKONIUM CHLORIDE 0.01 g/59 g
INACTIVE INGREDIENTS: FD&C RED NO. 40; FD&C BLUE NO. 1; FD&C YELLOW NO. 5; SODIUM HYDROXIDE; WATER; PROPYLENE GLYCOL; COCETH-7 CARBOXYLIC ACID; CHLOROPROPYLATE; PEG-40 CASTOR OIL; PPG-1-PEG-9 LAURYL GLYCOL ETHER; PHENOXYETHANOL; D&C RED NO. 33

Active Ingredient

Benzalkonium Chloride 0.01%

Purpose: Antibacterial

Use

To decrease bacteria on the skin that could cause disease.

Keep out of reach of children.

Warnings

- for external use only-hands.
- keep out of eyes. avoid contact with broken skin.
- stop use and ask a Doctor if irritation or redness develops.
- do not inhale or ingest. if swallowed, get medical help or contact a poison control center right away.

Directions

- Rub a dime sized drop into hands.
- For children under 6 use under adult supervision.

Inactive Ingredients

water (aqua/eau), coceth-7, PPG-1-PEG-9 lauryl glycol ether, triethanolamine, PEG-40 hydrogenated castor oil, chloropropylate, fragrance (parfum).

INDICATIONS AND USAGE

Frozen Grape Hand Sanitizer

2 FL OZ (59mL)